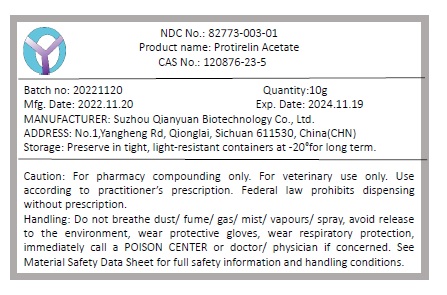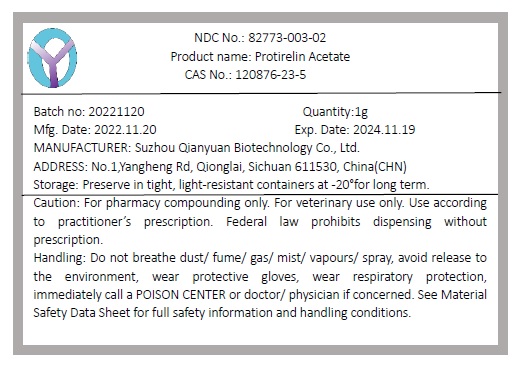 DRUG LABEL: Protirelin Acetate
NDC: 82773-003 | Form: POWDER
Manufacturer: Suzhou Qianyuan Biotechnology Co., Ltd.
Category: other | Type: BULK INGREDIENT - ANIMAL DRUG
Date: 20221130

ACTIVE INGREDIENTS: PROTIRELIN 1 g/1 g

Protirelin Acetate